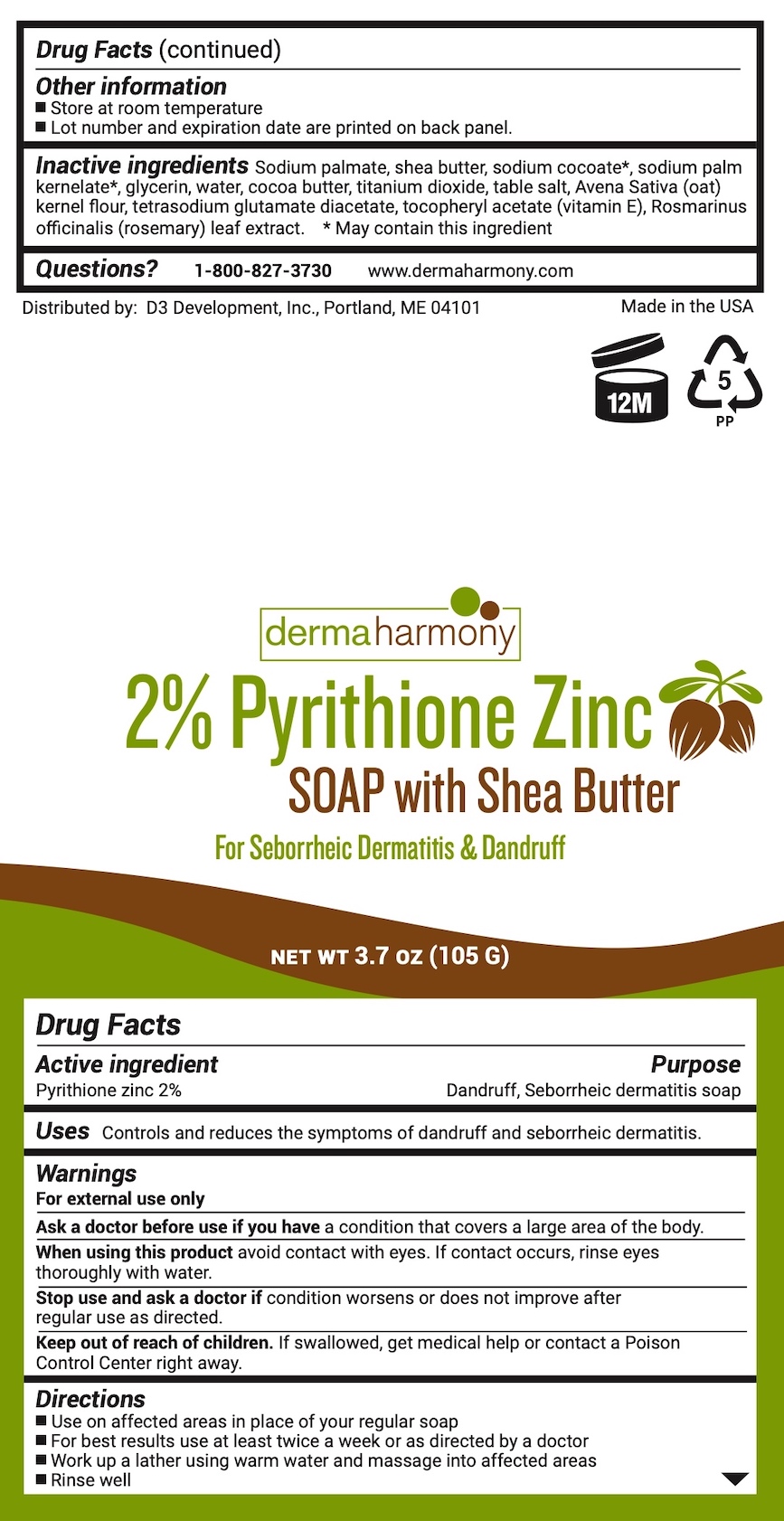 DRUG LABEL: Dermaharmony Pyrithione Zinc
NDC: 71819-017 | Form: SOAP
Manufacturer: D3 Development, Inc.
Category: otc | Type: HUMAN OTC DRUG LABEL
Date: 20241220

ACTIVE INGREDIENTS: PYRITHIONE ZINC 2 g/100 g
INACTIVE INGREDIENTS: SHEA BUTTER; COCOA BUTTER; SODIUM CHLORIDE; TITANIUM DIOXIDE; WATER; SODIUM COCOATE; GLYCERIN; OATMEAL; SODIUM PALM KERNELATE; TETRASODIUM GLUTAMATE DIACETATE; SODIUM PALMATE; .ALPHA.-TOCOPHEROL ACETATE, D-; ROSEMARY

2% Pyrithione Zinc Bar with Shea Butter

Drug Facts

Active ingredient

Pyrithione zinc 2%

Purpose

Dandruff, Seborrheic dermatitis soap

Uses

Controls and reduces the symptoms of dandruff and seborrheic dermatitis.

Warnings

For external use only

Ask a doctor before use if you havea condition that covers a large area of the body.

WHEN USING

When using this productavoid contact with eyes. If contact occurs, rinse eyes thoroughly with water.

Stop use and ask a doctor ifcondition worsens or does not improve after regular use as directed.

Keep out of reach of children.If swallowed, get medical help or contact a Poison Control Center right away.

Directions

- Use on affected areas in place of your regular soap
- For best results use at least twice a week or as directed by a doctor
- Work up a lather using warm water and massage into affected areas
- Rinse well

Other information

- Store at room temperature
- Lot number and expiration date are printed on back panel.

Inactive ingredients

Sodium palmate, shea butter, sodium cocoate*, sodium palm kernelate*, glycerin, water, cocoa butter, titanium dioxide, Avena Sativa (oat) kernel flour, tetrasodium glutamate diacetate, tocopheryl acetate (vitamin E), Rosmarinus officinalis (rosemary) leaf extract. *May contain this ingredient

Questions?

1-800-827-3730

www.dermaharmony.com

Distributed by:

D3 Development, Inc., Portland, ME 04101

Made in the USA

PACKAGE LABEL

dermaharmony

2% Pyrithione Zinc SOAP with Shea Butter

For Seborrheic Dermatitis & Dandruff

NET WT 3.7 OZ (105 G)